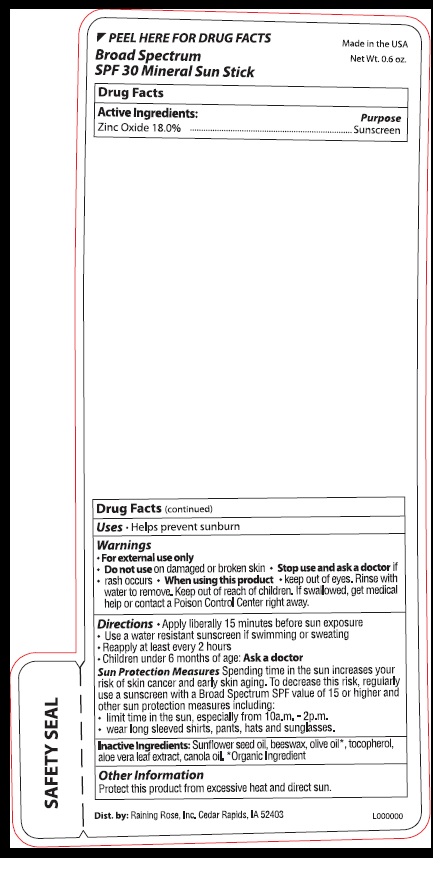 DRUG LABEL: SPF 30 Mineral Sun Stick
NDC: 65692-0848 | Form: STICK
Manufacturer: Raining Rose, Inc.
Category: otc | Type: HUMAN OTC DRUG LABEL
Date: 20190823

ACTIVE INGREDIENTS: ZINC OXIDE 3.06 g/17 g
INACTIVE INGREDIENTS: SUNFLOWER OIL; YELLOW WAX; OLIVE OIL; TOCOPHEROL; ALOE VERA LEAF; CANOLA OIL

SPF 30 Mineral Sun Stick

DRUG FACTS

Active Ingredients:

Zinc Oxide 18.0%

Purpose

Sunscreen

Uses

- Helps prevent sunburn

Warnings

- For External Use Only

- Do not use on damaged or broken skin

Stop use and as a doctor if • rash occurs

When using this product • Keep out of eyes. Rinse well with water to remove.

Keep out of reach of children.

If swallowed, get medical help or call a Poison Control Center right away.

DOSAGE AND ADMINISTRATION

Directions •Apply liberally 15 minutes before sun exposure
• Use a water resistant sunscreen if swimming or sweating

• Reapply at least every 2 hours
• Children under 6 months of age: Ask a doctor

Sun Protection Measures Spending time in the sun increases your
risk of skin cancer and early skin aging. To decrease this risk, regularly
use a sunscreen with a Broad Spectrum SPF value of 15 or higher and
other protection measures including:
• limit time in the sun, especially from 10a.m. - 2p.m.
• wear long sleeved shirts, pants, hat, and sunglasses.

INACTIVE INGREDIENT

Inactive Ingredients: Sunflower Seed Oil*, Beeswax*, Olive Oil*, Tocopherol,

aloe vera leaf extract, canola oil. *Organic Ingredient

Other Information: Protect this product from excessive heat and direct sun.

Product Package Labeling

◀ PEEL HERE FOR DRUG FACTS

Broad Spectrum

SPF 30 Mineral Sun Stick

Made in the USA

Net Wt. 0.6.oz.

Dist. by: Raining Rose, Inc., Cedar Rapids, IA 52403

L000000

SAFETY SEAL

res